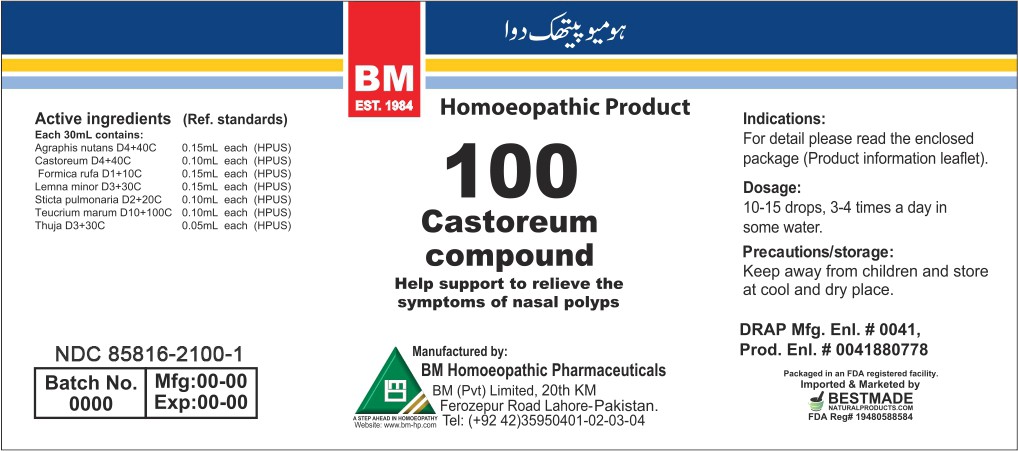 DRUG LABEL: CASTOREUM COMPOUND
NDC: 85816-2100 | Form: LIQUID
Manufacturer: BM Private Limited
Category: homeopathic | Type: HUMAN OTC DRUG LABEL
Date: 20250827

ACTIVE INGREDIENTS: HYACINTHOIDES NON-SCRIPTA WHOLE 40 [hp_C]/1 mL; LEMNA MINOR WHOLE 30 [hp_C]/1 mL; CASTOR CANADENSIS SCENT GLAND SECRETION 40 [hp_C]/1 mL; FORMICA RUFA 10 [hp_C]/1 mL; LOBARIA PULMONARIA 20 [hp_C]/1 mL; TEUCRIUM MARUM WHOLE 100 [hp_C]/1 mL; THUJA OCCIDENTALIS LEAFY TWIG 30 [hp_C]/1 mL
INACTIVE INGREDIENTS: ALCOHOL 0.96 mL/1 mL

BM HOMEOPATHIC LIQUID CASTOREUM COMPOUND/ BM100

DOSAGE AND ADMINISTRATION

10-15 drops, 3-4 times a day in some water

INACTIVE INGREDIENT

Alcohol

INDICATIONS AND USAGE

For detail, please read the enclosed package (product information leaflet)

PURPOSE

For detail, please read the enclosed package (product information leaflet)

WARNINGS

Precautions/storage:
Keep away from children and store at cool and dry place.

KEEP OUT OF REACH OF CHILDREN

Precautions/storage:
Keep away from children and store at cool and dry place.

ACTIVE INGREDIENT

Agraphis Nutans, Castoreum, Formica Rufa, Lemna Minor, Sanguinaria Nitricum, Sticta Pul, Teucrium Marum, Thuja